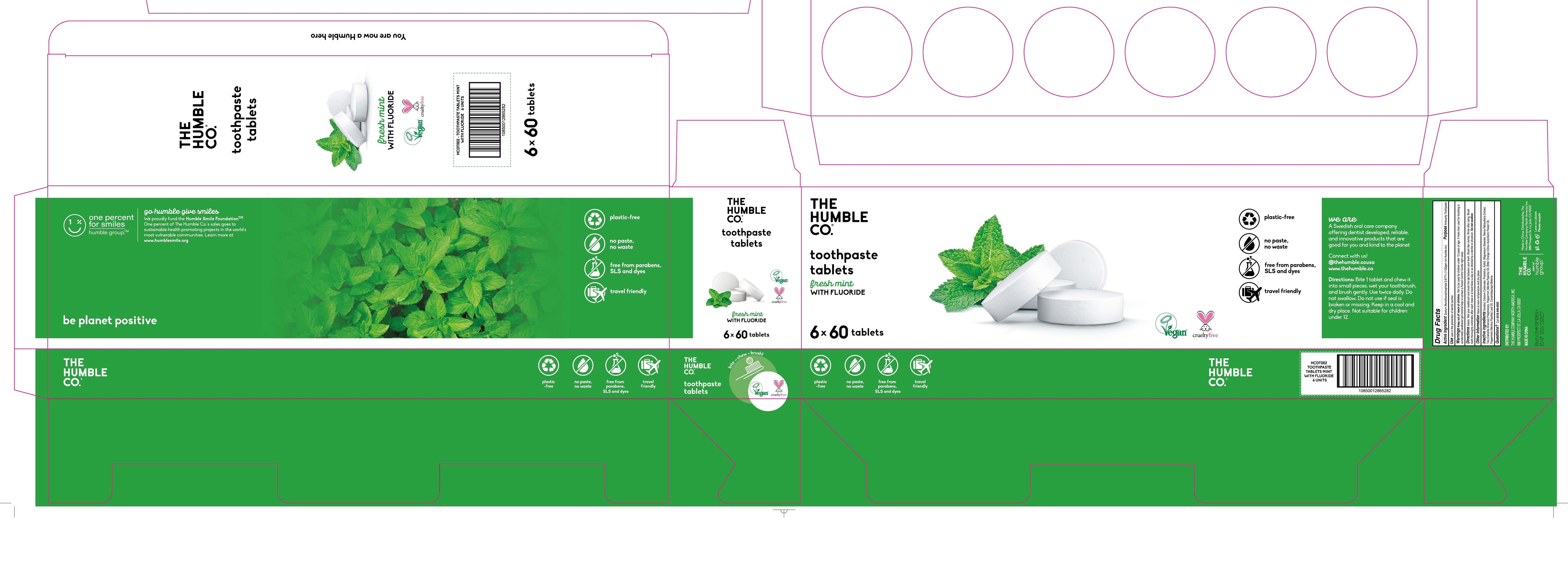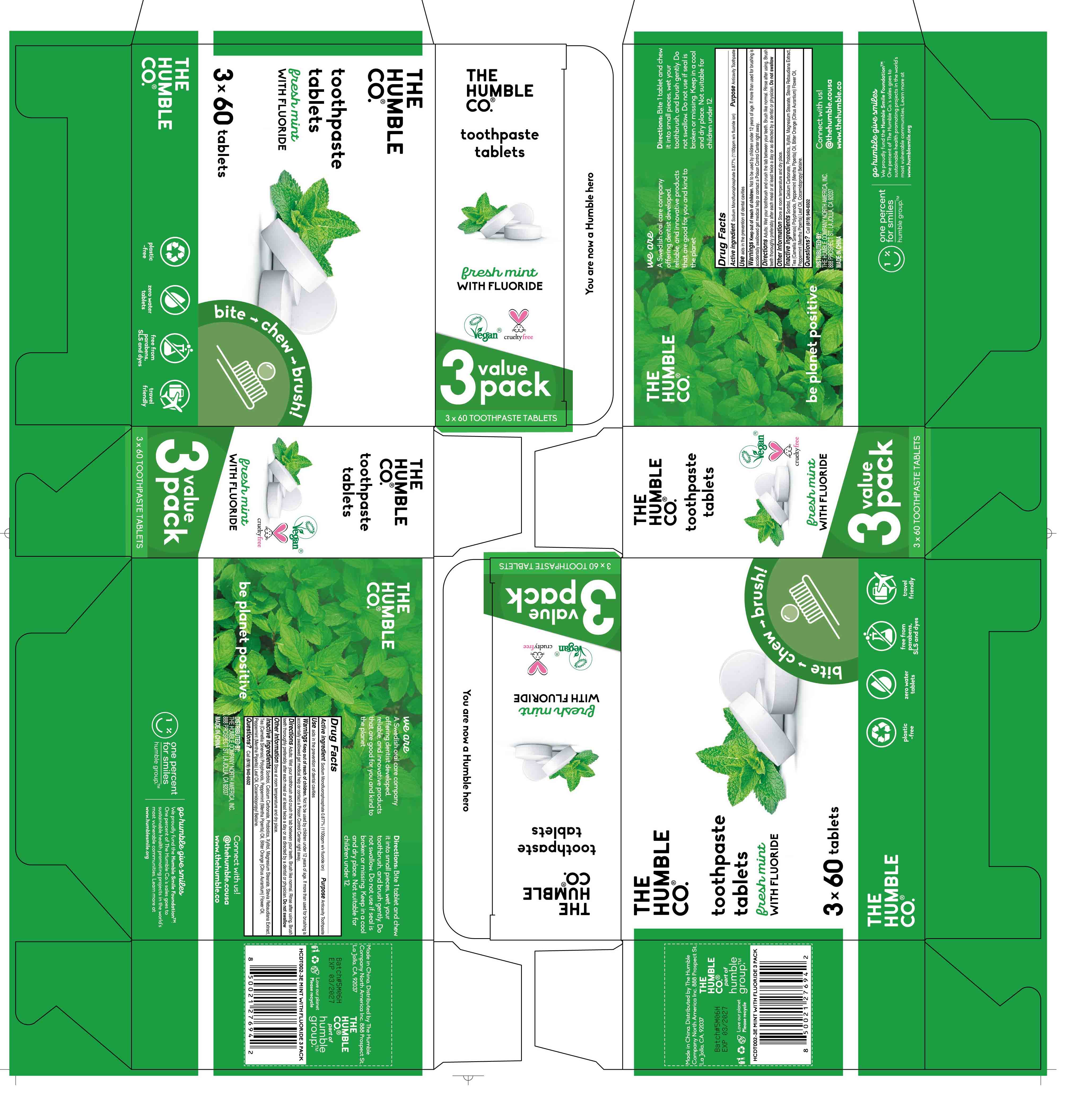 DRUG LABEL: Tooth
NDC: 85346-001 | Form: TABLET
Manufacturer: Henan Dailygreen Cosmetics Supplies Co.,Ltd.
Category: otc | Type: HUMAN OTC DRUG LABEL
Date: 20250313

ACTIVE INGREDIENTS: SODIUM MONOFLUOROPHOSPHATE 0.877 g/100 1
INACTIVE INGREDIENTS: STEVIA REBAUDIANA WHOLE; SORBITOL; CITRUS AURANTIUM AMARA (BITTER ORANGE) FLOWER OIL; CAMELLIA SINENSIS LEAF; XYLITOL; MAGNESIUM STEARATE; COCAMIDOPROPYL BETAINE; MENTHA PIPERITA (PEPPERMINT) OIL; MENTHA PIPERITA (PEPPERMINT) LEAF; CALCIUM CARBONATE

85346-001

ACTIVE INGREDIENT

Sodium Monofluorophosphate 0.877% (1100ppm w/v fluoride ion)

Purpose

Anticavity Toothpaste

Use

aids in the prevention of dental cavities

Warnings

Keep out of reach of children. Not to be used by children under 12 years of age.If more than used for brushing is accidentally swallowed get medical help or contact a Poison Control Center right away.

DO NOT USE

Do not swallow. Do not use if seal is broken or missing. Not suitable for children under 12.

WHEN USING

N/A

STOP USE

N/A

Keep out of reach of children.

Directions

Adults: Wet your toothbrush and crush the tab between your teeth. Brush like normal. Rinse after using. Brush teeth thoroughly preferably after each meal or at least twice a day or as directed by a dentist or physician. Do not swallow

Directions: Bite 1 tablet and chew it into small pieces, wet your toothbrush, and brush gently. Do not swallow. Do not use if seal is broken or missing. Keep in a cool and dry place. Not suitable for children under 12.

STORAGE AND HANDLING

Store at room temperature and dry place.

INACTIVE INGREDIENT

Inactive ingredients: Sorbitol, Calcium Carbonate, Probiotics, Xylitol, Magnesium Stearate, Stevia Rebaudiana Extract,Tea (Camellia Sinensis) Polyphenols, Peppermint (Mentha Piperita) Oil, Bitter Orange (Citrus Aurantium) Flower Oil, Peppermint (Mentha Piperita) Leaf Oil, Cocamidopropyl Betaine.